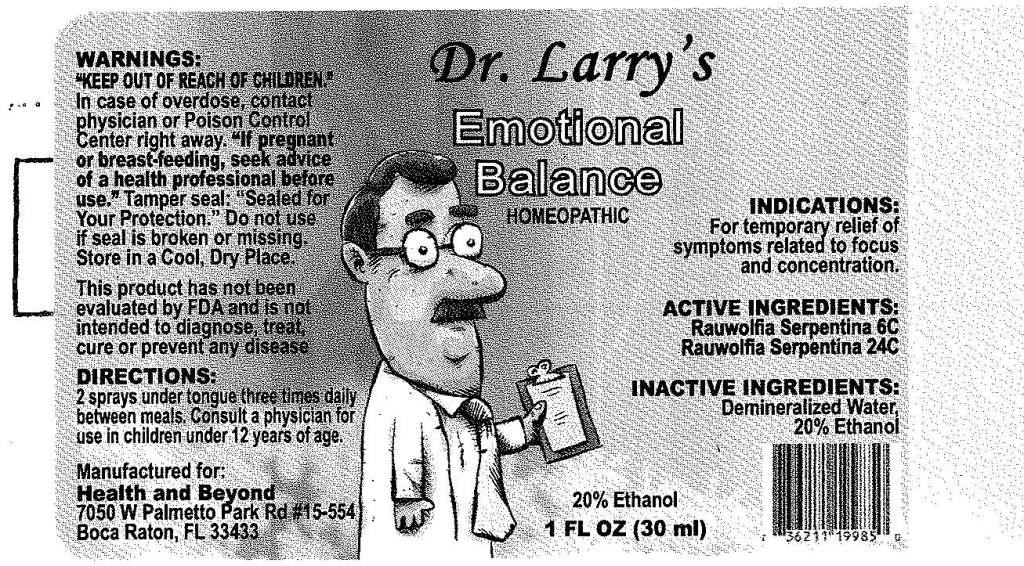 DRUG LABEL: Emotional Balance
NDC: 57520-0386 | Form: SPRAY
Manufacturer: Apotheca Company
Category: homeopathic | Type: HUMAN OTC DRUG LABEL
Date: 20101230

ACTIVE INGREDIENTS: RAUWOLFIA SERPENTINA 24 [hp_C]/1 mL
INACTIVE INGREDIENTS: WATER; ALCOHOL

Emotional Balance

ACTIVE INGREDIENT: Rauwolfia serpentina 6C, 24C.

PURPOSE

INDICATIONS: For temporary relief of symptoms related to focus and concentration.

WARNINGS

WARNINGS: Keep out of reach of children. In case of overdose, contact physician or Poison Control Center right away.

If pregnant or breast-feeding, seek advice of a health professional before use.

Tamper seal: "Sealed for Your Protection." Do not use if seal is broken or missing. Store in a cool, dry place.

DOSAGE AND ADMINISTRATION

DIRECTIONS: 2 sprays under tongue three times daily between meals. Consult a physician for use in children under 12 years of age.

INACTIVE INGREDIENTS: Demineralized water, 20% Ethanol.

KEEP OUT OF REACH OF CHILDREN. In case of overdose, contact physician or Poison Control Center right away.

INDICATIONS AND USAGE

INDICATIONS: For temporary relief of symptoms related to focus and concentration.

QUESTIONS

Manufactured for:

Health and Beyond

7050 W Palmetto Park Rd

#15-554

Boca Raton, FL33433

PACKAGE LABEL

Dr Larry's

EMOTIONAL BALANCE

HOMEOPATHIC

1 FL OZ (30 ML)